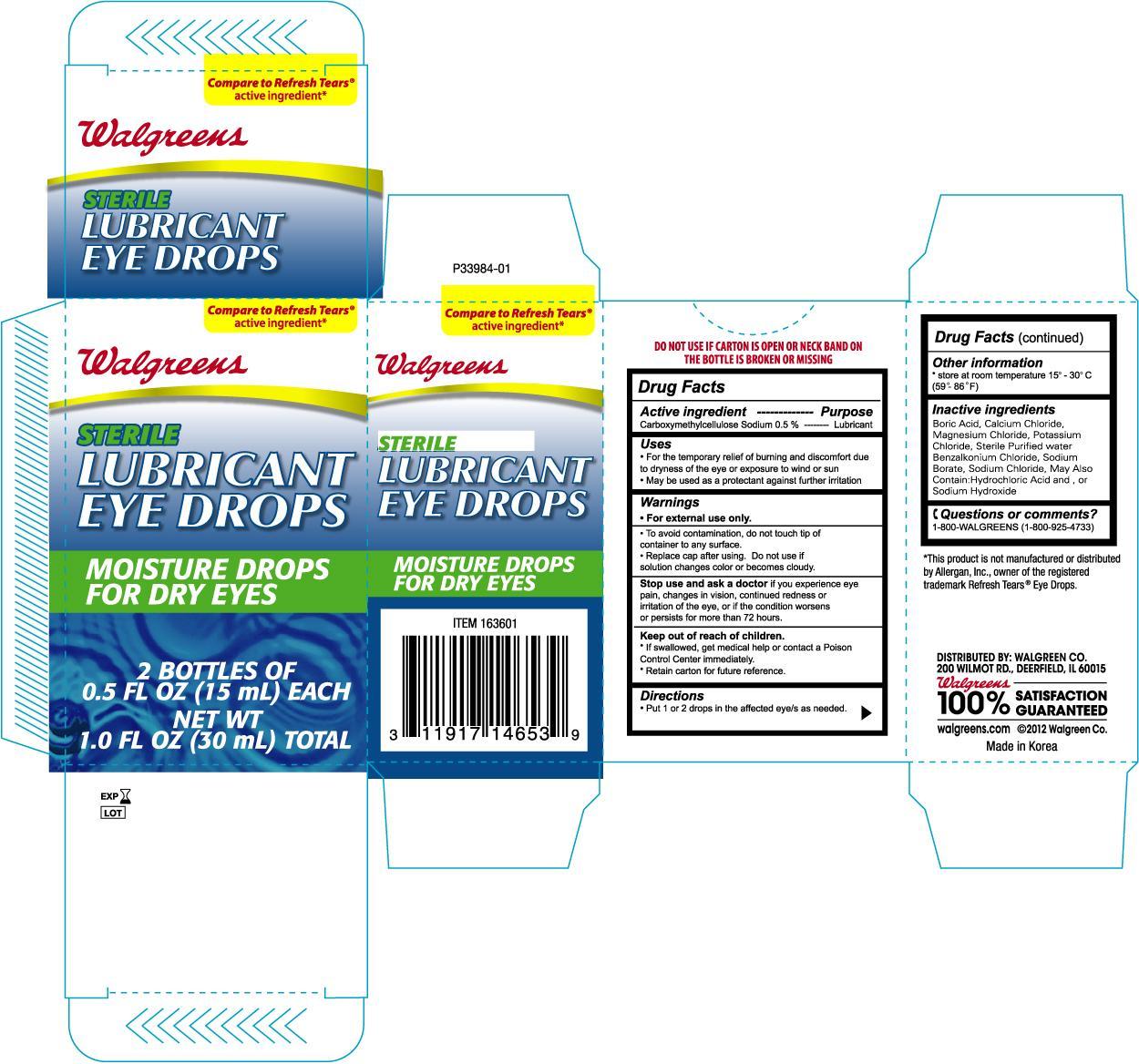 DRUG LABEL: WALGREENS LUBRICANT EYE 
NDC: 0363-1466 | Form: SOLUTION
Manufacturer: WALGREEN COMPANY
Category: otc | Type: HUMAN OTC DRUG LABEL
Date: 20120930

ACTIVE INGREDIENTS: CARBOXYMETHYLCELLULOSE SODIUM 5 mg/1 mL
INACTIVE INGREDIENTS: BORIC ACID; CALCIUM CHLORIDE; MAGNESIUM CHLORIDE; POTASSIUM CHLORIDE; BENZALKONIUM CHLORIDE; SODIUM BORATE; SODIUM CHLORIDE; WATER

Drug Facts

Active ingredient Purpose

Carboxymethylcellulose Sodium 0.5%......................................Lubricant

Uses

- For the temporary relief of burning and discomfort due to dryness of the eye or exposure to wind or sun
- May be used as a protectant against further irritation

Warnings

For external use only

DO NOT USE

To avoid contamination, do not touch tip of container to any surface

Replace cap after using. Do not use if solution changes color or becomes cloudy.

Stop use and ask a doctor if you experience eye pain, changes in vision, continued redness or irritation of the eye, or if the condition worsens or persists for more than 72 hours.

Keep out of the reach of children.

- If swallowed, get medical help or contact a Poison Control Center immediately
- Retain carton for future reference.

Directions

- Put 1 or 2 drops in the affected eye/s as needed

Other information

- store at room temperature 15o to 30oC (59o to 86oF)

INACTIVE INGREDIENT

Boric Acid, Calcium Chloride, Magnesium Chloride, Potassium Chloride, Sterile Purified Water, Benzalkonium Chloride, Sodium Borate, Sodium Chloride

DOSAGE AND ADMINISTRATION

DISTRIBUTED BY: WALGREEN CO.

200 WILMOT RD., DEERFIELD, IL 60015

walgreens.com

Made in Korea